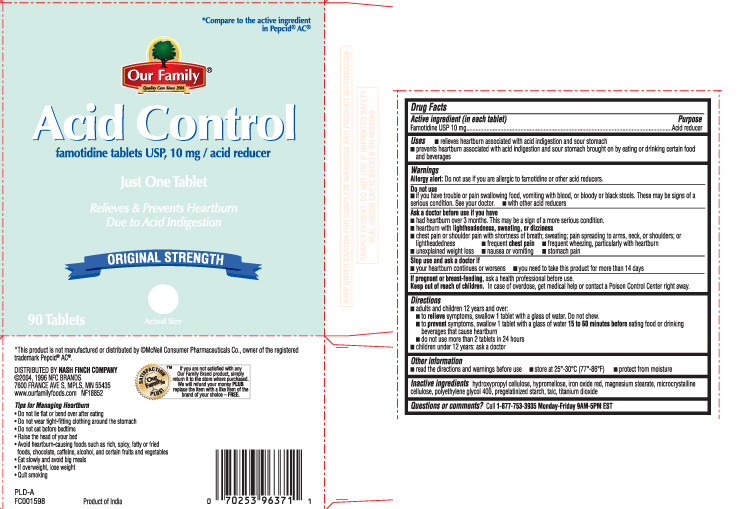 DRUG LABEL: Famotidine
NDC: 70253-128 | Form: TABLET
Manufacturer: OUR FAMILY (Nash Finch Company)
Category: otc | Type: HUMAN OTC DRUG LABEL
Date: 20131009

ACTIVE INGREDIENTS: FAMOTIDINE 10 mg/1 1
INACTIVE INGREDIENTS: HYDROXYPROPYL CELLULOSE (TYPE H); HYPROMELLOSES; FERRIC OXIDE RED; MAGNESIUM STEARATE; CELLULOSE, MICROCRYSTALLINE; POLYETHYLENE GLYCOL 400; STARCH, CORN; TALC; TITANIUM DIOXIDE

Drug Facts

Active ingredient (in each tablet)

Famotidine USP 10 mg

Purpose

Acid reducer

Uses

- relieves heartburn associated with acid indigestion and sour stomach
- prevents heartburn associated with acid indigestion and sour stomach brought on by eating or drinking certain food and beverages

Warnings

Allergy alert: Do not use if you are allergic to famotidine or other acid reducers.

Do not use

- if you have trouble or pain swallowing food, vomiting with blood, or bloody or black stools. These may be signs of a serious condition. See your doctor.
- with other acid reducers

Ask a doctor before use if you have

- had heartburn over 3 months. This may be a sign of a more serious condition.
- heartburn with lightheadedness, sweating, or dizziness
- chest pain or shoulder pain with shortness of breath; sweating; pain spreading to arms, neck, or shoulders; or lightheadedness
- frequent chest pain
- frequent wheezing, particularly with heartburn
- unexplained weight loss
- nausea or vomiting
- stomach pain

Stop use and ask a doctor if

- your heartburn continues or worsens
- you need to take this product for more than 14 days

If pregnant or breast-feeding,

ask a health professional before use.

Keep out of reach of children.

In case of overdose, get medical help or contact a Poison Control Center right away.

Directions

- adults and children 12 years and over:
  - to relieve symptoms, swallow 1 tablet with a glass of water. Do not chew.
  - to prevent symptoms, swallow 1 tablet with a glass of water 15 to 60 minutes before eating food or drinking beverages that cause heartburn
  - do not use more than 2 tablets in 24 hours
- children under 12 years: ask a doctor

Other information

- read the directions and warnings before use
- store at 25°-30°C (77°-86°F)
- protect from moisture

Inactive ingredients

hydroxypropyl cellulose, hypromellose, iron oxide red, magnesium stearate, microcrystalline cellulose, polyethylene glycol 400, pregelatinized starch, talc, titanium dioxide

Questions or comments?

Call 1-877-753-3935 Monday-Friday 9AM-5PM EST

Principal Display Panel

*Compare to the active ingredient in Pepcid® AC®

Acid Control

famotidine tablets USP, 10 mg / acid reducer

Just One Tablet

Relieves & Prevents Heartburn Due to Acid Indigestion

ORIGINAL STRENGTH

Tablets

*This product is not manufactured or distributed by ©McNeil Consumer Pharmaceuticals Co., owner of the registered trademark Pepcid® AC®.

DISTRIBUTED BY NASH FINCH COMPANY

7600 FRANCE AVE S, MPLS, MN 55435

KEEP OUTER CARTON FOR COMPLETE WARNINGS AND PRODUCT INFORMATION.

TAMPER EVIDENT: DO NOT USE IF IMPRINTED SAFETY SEAL UNDER CAP IS BROKEN OR MISSING.

Tips for Managing Heartburn

- Do not lie flat or bend over after eating
- Do not wear tight-fitting clothing around the stomach
- Do not eat before bedtime
- Raise the head of your bed
- Avoid heartburn-causing foods such as rich, spicy, fatty or fried foods, chocolate, caffeine, alcohol, and certain fruits and vegetables
- Eat slowly and avoid big meals
- If overweight, lose weight
- Quit smoking

Product of India

Product Label

Our Family Acid Control Tablet